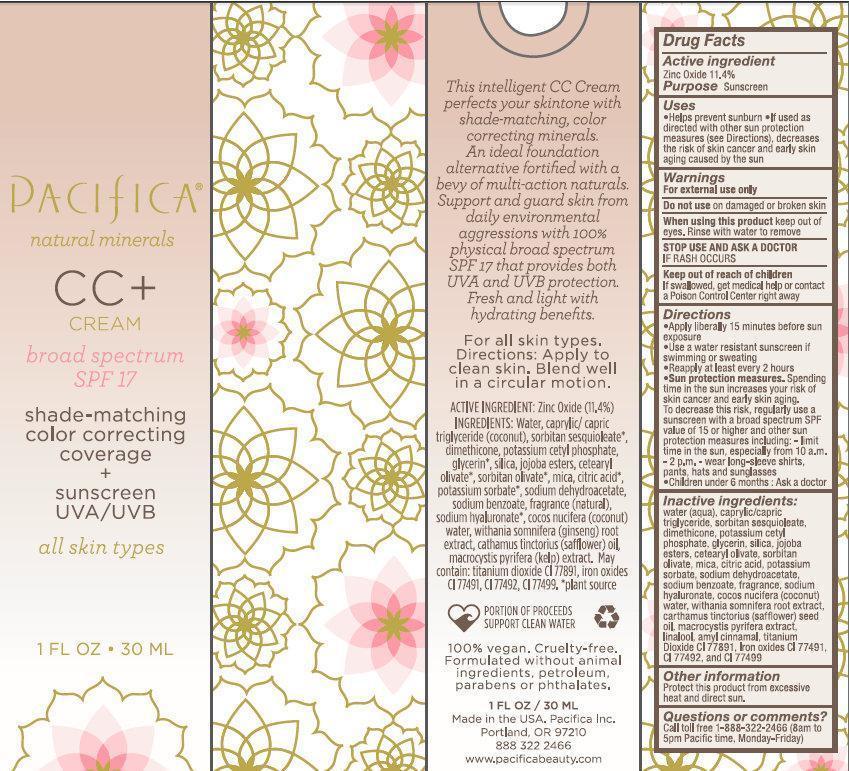 DRUG LABEL: Pacifica CC broad spectrum SPF 17 MEDIUM
NDC: 61197-001 | Form: CREAM
Manufacturer: Pacifica Beauty, LLC
Category: otc | Type: HUMAN OTC DRUG LABEL
Date: 20191210

ACTIVE INGREDIENTS: ZINC OXIDE 114 mg/1 mL
INACTIVE INGREDIENTS: WATER; MEDIUM-CHAIN TRIGLYCERIDES; SORBITAN SESQUIOLEATE; POTASSIUM CETYL PHOSPHATE; GLYCERIN; SILICON DIOXIDE; ETHYL JOJOBATE; CETEARYL OLIVATE; SORBITAN OLIVATE; MICA; CITRIC ACID MONOHYDRATE; POTASSIUM SORBATE; SODIUM DEHYDROACETATE; SODIUM BENZOATE; HYALURONATE SODIUM; COCONUT JUICE; WITHANIA SOMNIFERA ROOT; SAFFLOWER OIL; MACROCYSTIS PYRIFERA; .ALPHA.-AMYLCINNAMALDEHYDE; TITANIUM DIOXIDE; FERRIC OXIDE RED; FERRIC OXIDE YELLOW; FERROSOFERRIC OXIDE

Pacifica CC+ CREAM broad spectrum SPF 17 MEDIUM

Active ingredient

ZInc Oxide 11.4%

Purpose

Sunscreen

Uses

- Helps prevent sunburn
- If used as directed with other sun protection measures (see Directions), decreases the risk of skin cancer and early skin aging caused by the sun.

Warnings

For external use only

Do not use

on damaged or broken skin.

When using this product

keep out of eyes. Rinse with water to remove

STOP USE AND ASK A DOCTOR

IF RASH OCCURS

Keep out of reach of children

If swallowed, get medical help or contact a Poison Control Center right away.

Directions:

- Apply liberally 15 minutes before sun exposure
- Use a water resistant sunscreen if swimming or sweating
- Reapply at least every 2 hours
- Sun Protection Measures. Spending time in the sun increases your risk of skin cancer and early skin aging. To decrease this risk, regularly use a sunscreen with a broad spectrum SPF value of 15 or higher and other sun protection measures including:

- limit time in the sun, especially from 10 a.m. - 2 p.m.

- wear long-sleeved shirts, pants, hats and sunglasses

- Children under 6 months: Ask a doctor

Inactive ingredients:

water (aqua), caprylic/capric triglyceride, sorbitan sesquioleate, dimethicone, potassium cetyl phosphate, glycerin, silica, jojoba esters, ceteraryl olivate, sorbitan olivate, mica, citric acid, potassium sorbate, sodium dehydroacetate, sodium benzoate, fragrance, sodium hyaluronate, cocos nucifera (coconut) water, withania somnifera root extract, carthamus tinctorius (safflower) seed oil, macrocystis pyrifera extract, linalool, amyl cinnamal, titanium Dioxide, CI 77891, Iron oxides CI 77491, CI 77492, and CI77499

Other Information

Protect this product from excessive heat and direct sun

Questions or comments?

Call toll free 1-888-322-2466 (8am to 5pm Pacific time, Monday-Friday)